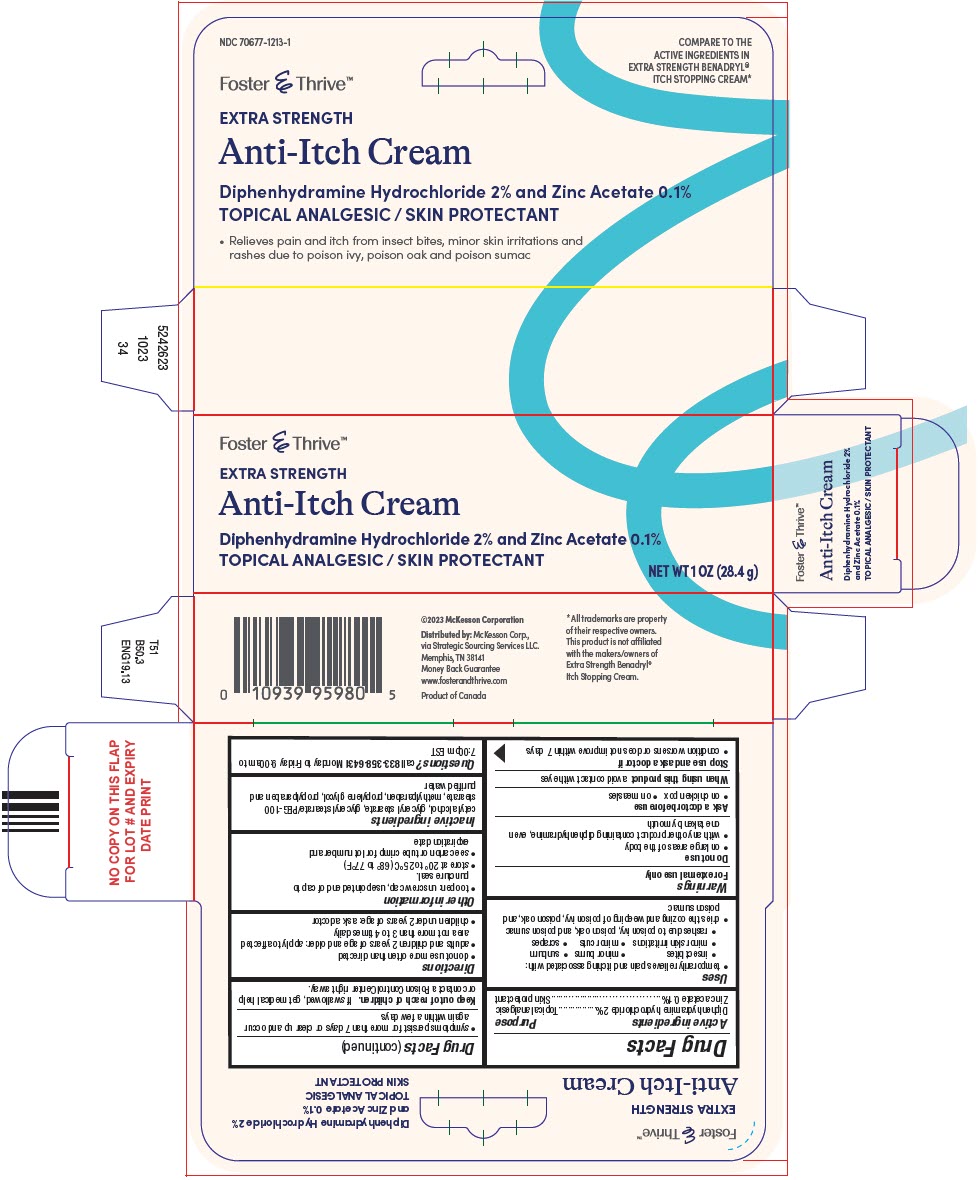 DRUG LABEL: Diphenhydramine Hydrochloride and Zinc Acetate
NDC: 70677-1213 | Form: CREAM
Manufacturer: STRATEGIC SOURCING SERVICES LLC
Category: otc | Type: HUMAN OTC DRUG LABEL
Date: 20250714

ACTIVE INGREDIENTS: DIPHENHYDRAMINE HYDROCHLORIDE 20 mg/1 g; ZINC ACETATE 1 mg/1 g
INACTIVE INGREDIENTS: CETYL ALCOHOL; GLYCERYL MONOSTEARATE; PEG-100 STEARATE; METHYLPARABEN; PROPYLENE GLYCOL; PROPYLPARABEN; WATER

Diphenhydramine Hydrochloride and Zinc Acetate

Drug Facts

ACTIVE INGREDIENT

Active ingredients | Purpose
Diphenhydramine hydrochloride 2% | Topical analgesic
Zinc acetate 0.1% | Skin protectant

Uses

- temporarily relieves pain and itching associated with:
  - insect bites
  - minor burns
  - sunburn
  - minor skin irritations
  - minor cuts
  - scrapes
  - rashes due to poison ivy, poison oak, and poison sumac
- dries the oozing and weeping of poison ivy, poison oak, and poison sumac

Warnings

For external use only

Do not use

- on large areas of the body
- with any other product containing diphenhydramine, even one taken by mouth

Ask a doctor before use

- on chicken pox
- on measles

When using this productavoid contact with eyes

Stop use and ask a doctor if

- condition worsens or does not improve within 7 days
- symptoms persist for more than 7 days or clear up and occur again within a few days

Keep out of reach of children.If swallowed, get medical help or contact a Poison Control Center right away.

Directions

- do not use more often than directed
- adults and children 2 years of age and older: apply to affected area not more than 3 to 4 times daily
- children under 2 years of age: ask a doctor

Other information

- to open: unscrew cap, use pointed end of cap to puncture seal.
- store at 20° to 25°C (68° to 77°F)
- see carton or tube crimp for lot number and expiration date

Inactive ingredients

cetyl alcohol, glyceryl stearate, glyceryl stearate/PEG-100 stearate, methylparaben, propylene glycol, propylparaben and purified water

Questions?

call 833-358-6431Monday to Friday 9:00am to 7:00pm EST

Distributed by:McKesson Corp.,
via Strategic Sourcing Services LLC.
Memphis, TN 38141

PRINCIPAL DISPLAY PANEL - 28.4 g Tube Carton

Foster & Thrive™

EXTRA STRENGTH

Anti-Itch Cream

Diphenhydramine Hydrochloride 2% and Zinc Acetate 0.1%

TOPICAL ANALGESIC / SKIN PROTECTANT

NET WT 1 OZ (28.4 g)